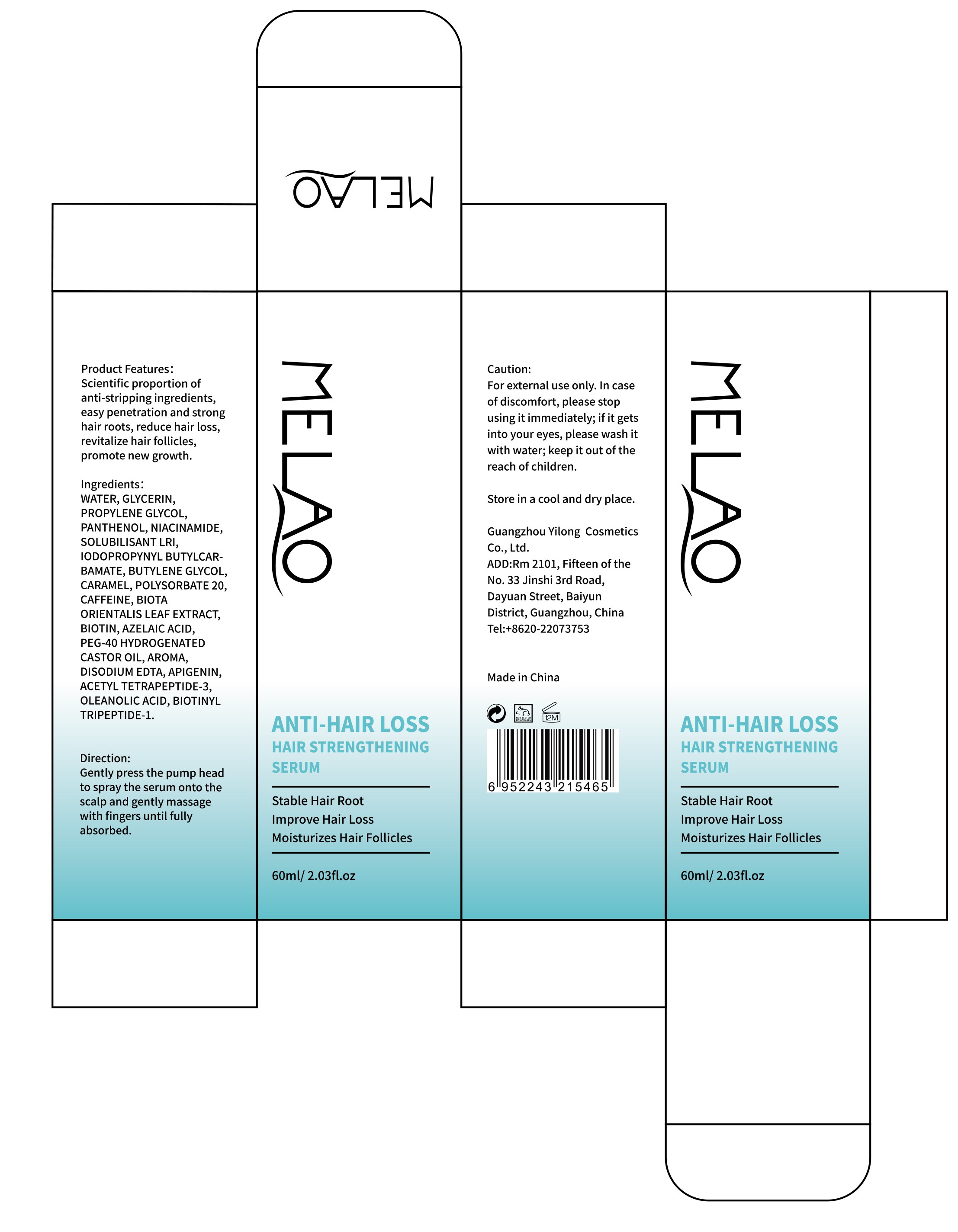 DRUG LABEL: ANTI HAIR LOSS HAIR STRENGTHENING SERUM
NDC: 84778-025 | Form: LIQUID
Manufacturer: Guangzhou Yixin Cross-border E-commerce Co., Ltd.
Category: otc | Type: HUMAN OTC DRUG LABEL
Date: 20241105

ACTIVE INGREDIENTS: NIACINAMIDE 10 g/60 mL
INACTIVE INGREDIENTS: PLATYCLADUS ORIENTALIS LEAF; OLEANOLIC ACID; BIOTINOYL TRIPEPTIDE-1; EGG SHELL MEMBRANE; BIOTIN; SURFOMER; EDETATE DISODIUM; IODOPROPYNYL BUTYLCARBAMATE; POLYSORBATE 20; ACETYL TETRAPEPTIDE-3; CARAMEL; GLYCOL; CAFFEINE; WATER; GLYCERIN; AZELAIC ACID; POLYOXYL 40 HYDROGENATED CASTOR OIL; PROPYLENE; BUTYLENE GLYCOL; APIGENIN

Active ingredients

NIACINAMIDE 5%

Purpose

Improve scalp health, reduce inflammation, and promote hair growth

Uses

Gently press the pumphead to spray the serumonto the scalp

Gently massage with fin-gers until fully absorbed

Warnings

For external use only

Do not use if

You have no famlly history of hair loss

your hair loss is sudden and/or patchy

you do not know the reason for your hair loss

you are under 18 years of age, Do not use on babies and children

your scalp is red, inflamed, infected, irritated, or painful

you use other medicines on the scalp

Ask a doctor before use if you have heart disease

Dosage and administration

For external use only.

Do not use

Stop use and ask a doctor if

chest pain, rapid heartbeat, faintness, or dizziness occurs

sudden, unexplained weight gain occurs

your hands or feet swell

scalp irritation or redness occurs

unwanted facial hair growth occurs

you do not see hair regrowth in 4 months

May be harmful if used when pregnant or breast-feeding.

Keep out of reach of children, lf swallowed, get medical help or contact a Poison Control Center right away.

When using section

do not apply on other parts of the body

avoid contact with the eyes. in case of accidental contact, rinse eyes with large amounts of cool tap water

some people have experienced changes in hair color and/or texture

it takes time to regrow hair. Results may occur at 2 months with twice a day usage. For some people, you may need to use this product for at least 4 months before you see results.

the amount of hair regrowth is different for each person. This product may not be suitable for all males or females

stop use

on broken or irritated scalp

Keep out of reach of children

If sxralowed, get medical help or contact a Poison Conirol Cenler ngiht away.

Inactive ingredients

WATER，GLYCERIN，PROPYLENE PANTHENOL，GLYCOL，SOLUBILISANT LRI，IODOPROPYNYL BUTYLCARBAMATE，BUTYLENE GLYCOL，CARAMEL，POLYSORBATE 20，CAFFEINE，BIOTA ORIENTALIS LEAF EXTRACT，BIOTIN，AZELAIC ACID，PEG-40 HYDROGENATED CASTOR OIL，AROMA，DISODIUM EDTA，APIGENIN，ACETYL TETRAPEPTIDE-3，OLEANOLIC ACID，BIOTINYLTRIPEPTIDE-1